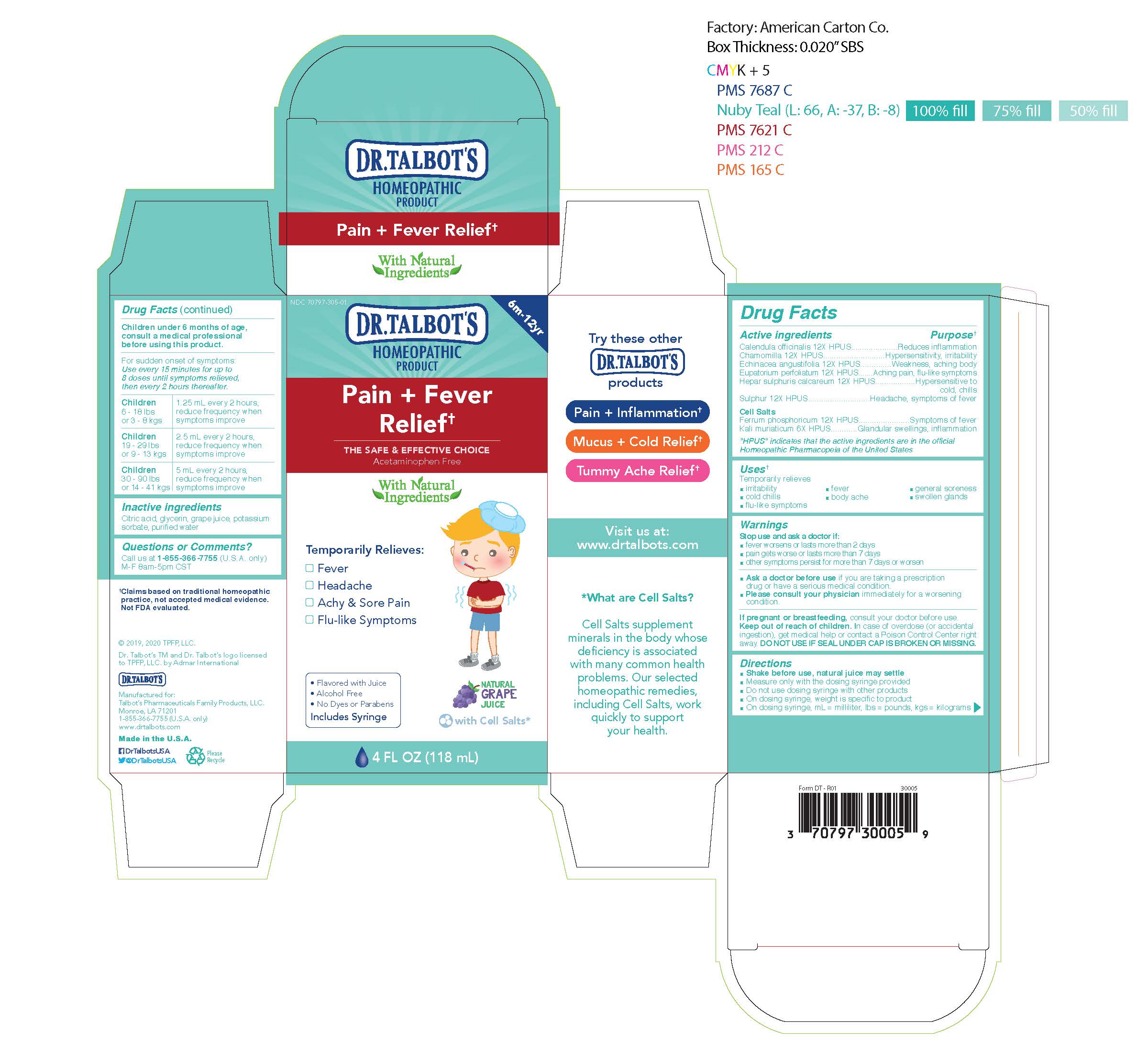 DRUG LABEL: Dr. Talbots Pain Fever Relief
NDC: 70797-315 | Form: LIQUID
Manufacturer: Talbot's Pharmaceuticals Family Products, LLC.
Category: homeopathic | Type: HUMAN OTC DRUG LABEL
Date: 20211005

ACTIVE INGREDIENTS: MATRICARIA CHAMOMILLA 12 [hp_X]/118 mL; EUPATORIUM PERFOLIATUM FLOWERING TOP 12 [hp_X]/118 mL; CALENDULA OFFICINALIS FLOWERING TOP 12 [hp_X]/118 mL; ECHINACEA ANGUSTIFOLIA 12 [hp_X]/118 mL; CALCIUM SULFIDE 12 [hp_X]/118 mL; POTASSIUM CHLORIDE 6 [hp_X]/118 mL; FERROSOFERRIC PHOSPHATE 12 [hp_X]/118 mL; COSMOS SULPHUREUS FLOWERING TOP 12 [hp_X]/118 mL
INACTIVE INGREDIENTS: CITRIC ACID MONOHYDRATE; GLYCERIN; CONCORD GRAPE JUICE; WATER; POTASSIUM SORBATE

Acitve Ingredients

Active Ingredients
Calendula officinalis 12X HPUS
Chamomilla 12X HPUS
Echinacea angustifolia 12X HPUS
Eupatorium perfoliatum 12X HPUS
Hepar sulphuris calcareum 12X HPUS
Sulphur 12X HPUS
Cell Salts
Ferrum phosphoricum 12X HPUS
Kali muriaticum 6X HPUS

Warnings

Stop use and ask doctor if:

- fever wosens or lasts more than 2 days
- pain gets worse or lasts more than 7 days
- other symptoms persist for more than 7 days or worsen
- Ask a doctor before use if you are taking a prescription drug or have a serious medical condition.
- Please consult your physician immediately for a worsening condition.

Pregnant or breastfeeding

If pregnant or breastfeeding, consult your doctor before use.

Keep out of reach of children. In case of overdoes (or accidental ingestion), get medical help or contact a Poison Control Center right away. DO NOT USE IF SEAL UNDER CAP IS BROKEN OR MISSING.

Directions

- Shake before use, natural juice may settle
- Measure only with the dosing syringe provided
- Do not use dosing syringe with other products
- On dosing syringe, weight is specific to product
- On dosing syringe, ml = milliliter, lbs = pounds, kgs = kilograms

Children under 6 months of age, consult a medical professional before using this product.

For sudden onset of symptoms: Use every 15 minutes for up to 8 doses until symptoms relieved, then every 2 hours thereafter.

Children 6 - 18 lbs or 3 - 8 kgs

1.25 ml every 2 hours, reduce frequency when symptoms improve

Children 19 - 29 lbs or 9 - 13 kgs

2.5 ml every 2 hours, reduce frequency when symptoms improve

Children 30 - 90 lbs or 14 - 41 kgs

5 ml every 2 hours, reduce frequency when symptoms improve

Inactive Ingredients

Citric acid, glycerin, grape juice, potassium sorbate, purified water

Questions

Questions or Comments?

Call us at 1-800-588-6227

M-F 8am-5pm CST

Purpose

Reduces inflammation

Hypersensitivity, irritability
Weakness, aching body
Aching pain, flu-like symptoms

Hypersensitive to cold, chills

Headache, symptoms of fever
Symptoms of fever
Glandular swellings, inflammation